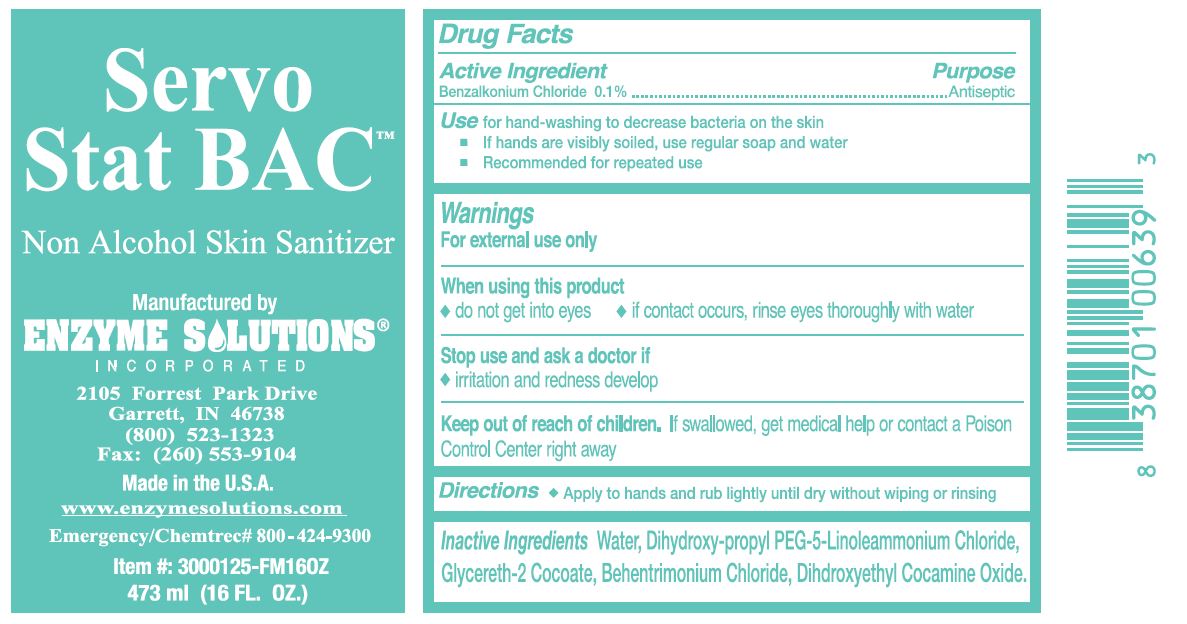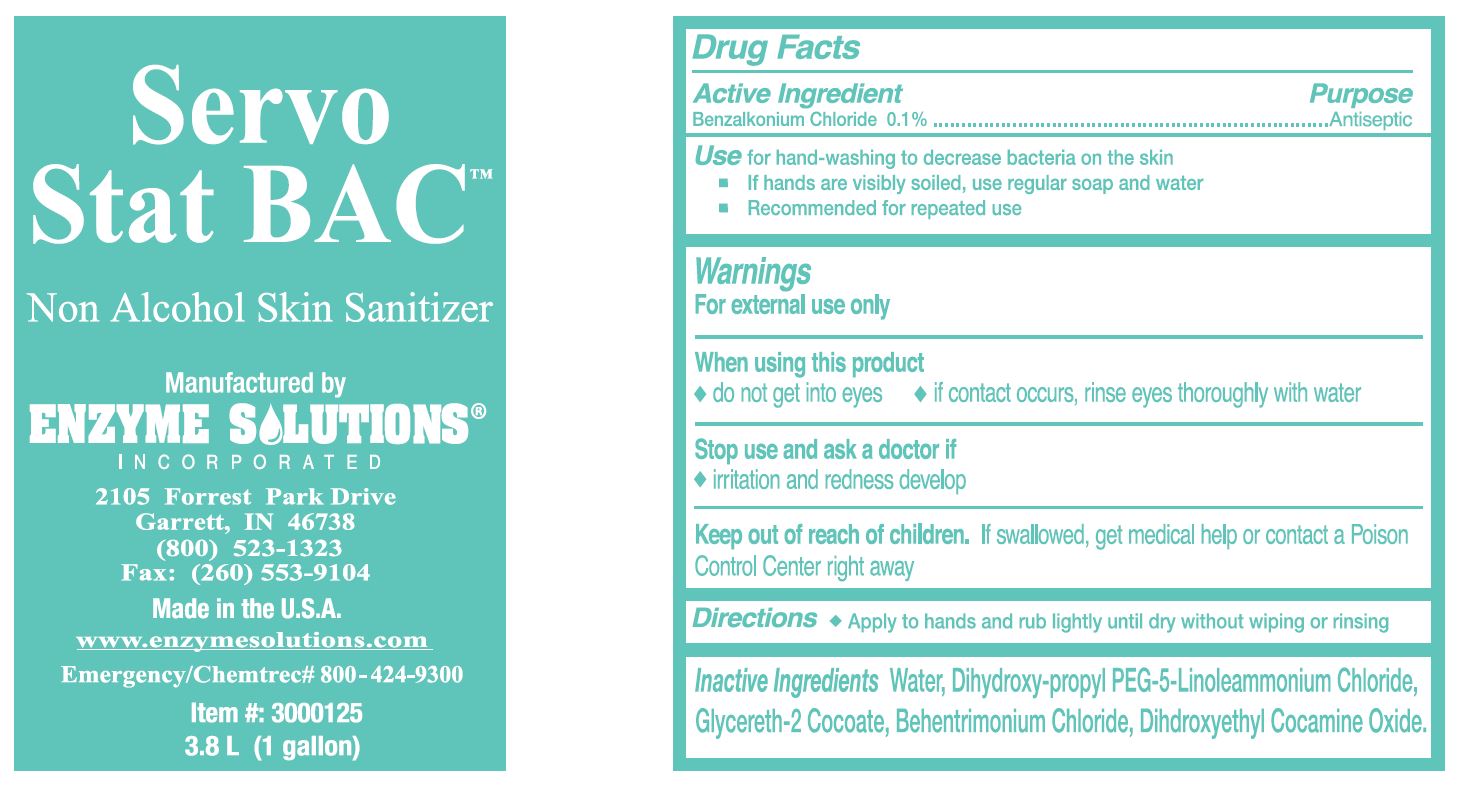 DRUG LABEL: Servo Stat BAC
NDC: 76378-023 | Form: LIQUID
Manufacturer: Enzyme Solutions, Inc.
Category: otc | Type: HUMAN OTC DRUG LABEL
Date: 20241126

ACTIVE INGREDIENTS: BENZALKONIUM CHLORIDE 1 mg/1 mL
INACTIVE INGREDIENTS: BEHENTRIMONIUM CHLORIDE; DIHYDROXYETHYL COCAMINE OXIDE; GLYCERETH-2 COCOATE; WATER; DIHYDROXYPROPYL PEG-5 LINOLEAMMONIUM CHLORIDE

76378-023

Active Ingredients

Benzalkonium Chloride 0.1%

Purpose

Antiseptic

Usefor hand-washing to decrease bacteria on the skin

- If hands are visibly soiled, use regular soap and water
- Recommended for repeated use

Warnings

For external use only

When using this product

- do not get into eyes
- if contact occurs, rinse eyes thoroughly with water

Stop use and ask a doctor if

- irritation and redness develop

Keep out of reach of children.

If swallowed, get medical help or contact a Poison Control Center right away

Directions

- Apply to hands and rub lightly until dry without wiping or rinsing

Inactive Ingredients

Water, Dihydroxy-propyl PEG-5-Linoleammonium Chloride, Glycereth-2 Cocoate, Behentrimonium Chloride, Dihdroxyethyl Cocamine Oxide.

PACKAGE LABEL

Servo

Stat BAC

Non Alcohol Skin Sanitizer

Manufactured by

Enzyme Solutions

Incorporated

2105 Forrest Park Drive

Garrett, IN 46738

(800) 523-1323

Fax (260) 553-9104

Made in the U.S.A.

www.enzymesolutions.com

Emergency Chemtrec# 800-424-9300

Item # 3000125-FM16OZ

473 ml (16 FL. OZ.)